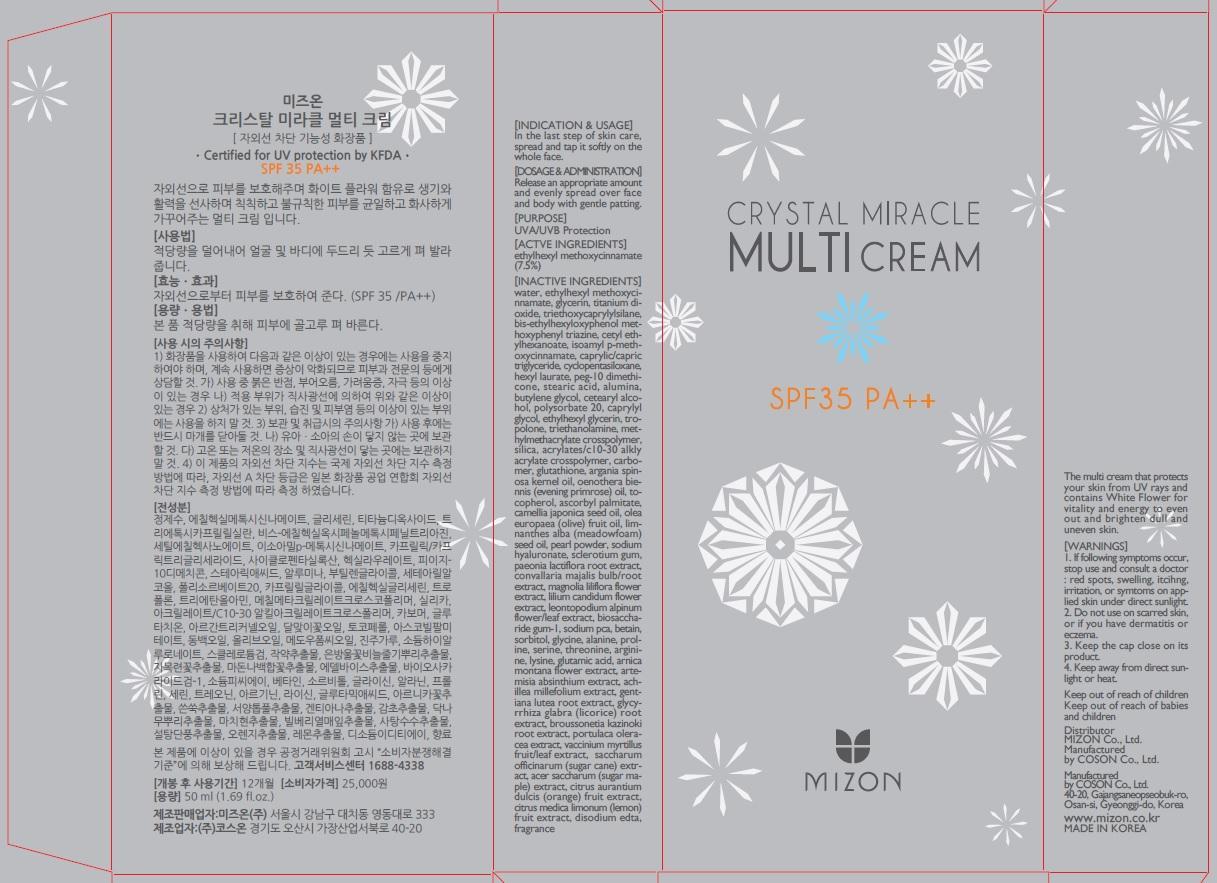 DRUG LABEL: CRYSTAL MIRACLE MULTI
NDC: 62171-040 | Form: CREAM
Manufacturer: Coson Co., Ltd.
Category: otc | Type: HUMAN OTC DRUG LABEL
Date: 20140418

ACTIVE INGREDIENTS: OCTINOXATE 3.75 mg/50 mL
INACTIVE INGREDIENTS: WATER; GLYCERIN

ACTIVE INGREDIENT

Actve Ingredient: ETHYLHEXYL METHOXYCINNAMATE 7.5%

INACTIVE INGREDIENT

Inactive Ingredients:
WATER, GLYCERIN, TITANIUM DIOXIDE, TRIETHOXYCAPRYLYLSILANE, BIS-ETHYLHEXYLOXYPHENOL METHOXYPHENYL TRIAZINE, CETYL ETHYLHEXANOATE, ISOAMYL p-METHOXYCINNAMATE, CAPRYLIC/CAPRIC TRIGLYCERIDE, CYCLOPENTASILOXANE, HEXYL LAURATE, PEG-10 DIMETHICONE, STEARIC ACID, ALUMINA, BUTYLENE GLYCOL, CETEARYL ALCOHOL, POLYSORBATE 20, CAPRYLYL GLYCOL, ETHYLHEXYL GLYCERIN, TROPOLONE, TRIETHANOLAMINE, METHYLMETHACRYLATE CROSSPOLYMER, SILICA, ACRYLATES/C10-30 ALKLY ACRYLATE CROSSPOLYMER, CARBOMER, GLUTATHIONE, ARGANIA SPINOSA KERNEL OIL, OENOTHERA BIENNIS (EVENING PRIMROSE) OIL, TOCOPHEROL, ASCORBYL PALMITATE, CAMELLIA JAPONICA SEED OIL, OLEA EUROPAEA (OLIVE) FRUIT OIL, LIMNANTHES ALBA (MEADOWFOAM) SEED OIL, PEARL POWDER, SODIUM HYALURONATE, SCLEROTIUM GUM, PAEONIA LACTIFLORA ROOT EXTRACT, CONVALLARIA MAJALIS BULB/ROOT EXTRACT, MAGNOLIA LILIFLORA FLOWER EXTRACT, LILIUM CANDIDUM FLOWER EXTRACT, LEONTOPODIUM ALPINUM FLOWER/LEAF EXTRACT, BIOSACCHARIDE GUM-1, SODIUM PCA, BETAIN, SORBITOL, GLYCINE, ALANINE, PROLINE, SERINE, THREONINE, ARGININE, LYSINE, GLUTAMIC ACID, ARNICA MONTANA FLOWER EXTRACT, ARTEMISIA ABSINTHIUM EXTRACT, ACHILLEA MILLEFOLIUM EXTRACT, GENTIANA LUTEA ROOT EXTRACT, GLYCYRRHIZA GLABRA(LICORICE)ROOT EXTRACT, BROUSSONETIA KAZINOKI ROOT EXTRACT, PORTULACA OLERACEA EXTRACT, VACCINIUM MYRTILLUS FRUIT/LEAF EXTRACT, SACCHARUM OFFICINARUM (SUGAR CANE) EXTRACT, ACER SACCHARUM (SUGAR MAPLE) EXTRACT, CITRUS AURANTIUM DULCIS (ORANGE) FRUIT EXTRACT, CITRUS MEDICA LIMONUM (LEMON) FRUIT EXTRACT, DISODIUM EDTA, FRAGRANCE

PURPOSE

Purpose: UVA/UVB Protection

WARNINGS

1. If following symptoms occur, stop use and consult a doctor : red spots, swelling, itcihng, irritation, or symtoms on applied skin under direct sunlight.
2. Do not use on scarred skin, or if you have dermatitis or eczema
3. Keep the cap close on its product
4. Keep away from direct sunlight or heat.

KEEP OUT OF REACH OF CHILDREN

Keep out of reach of babies and children

INDICATIONS AND USAGE

Indication and Usage:
In the last step of skin care, spread and tap it softly on the whole face.

DOSAGE AND ADMINISTRATION

Release an appropriate amount and evenly spread over face and body with gentle patting.